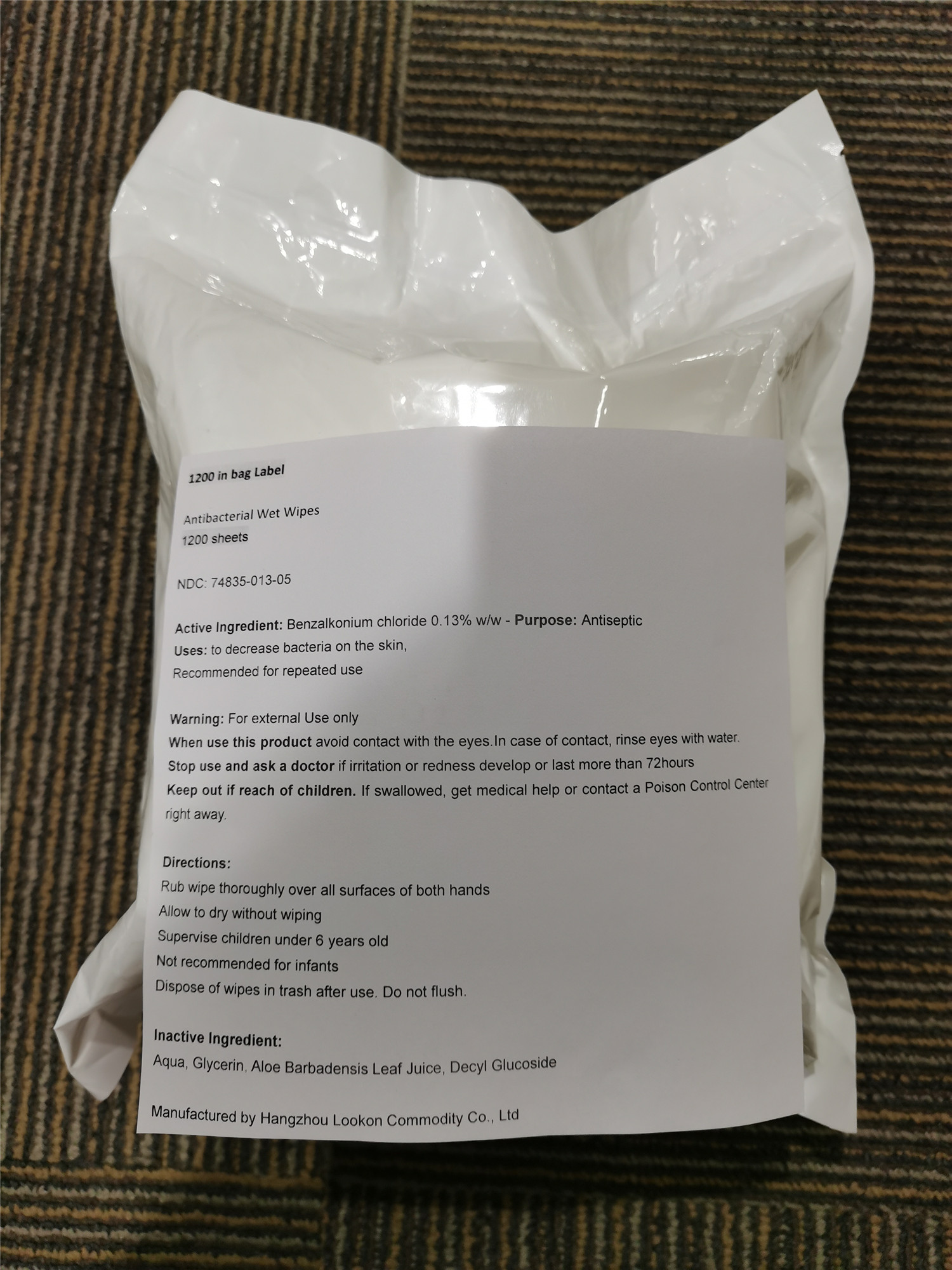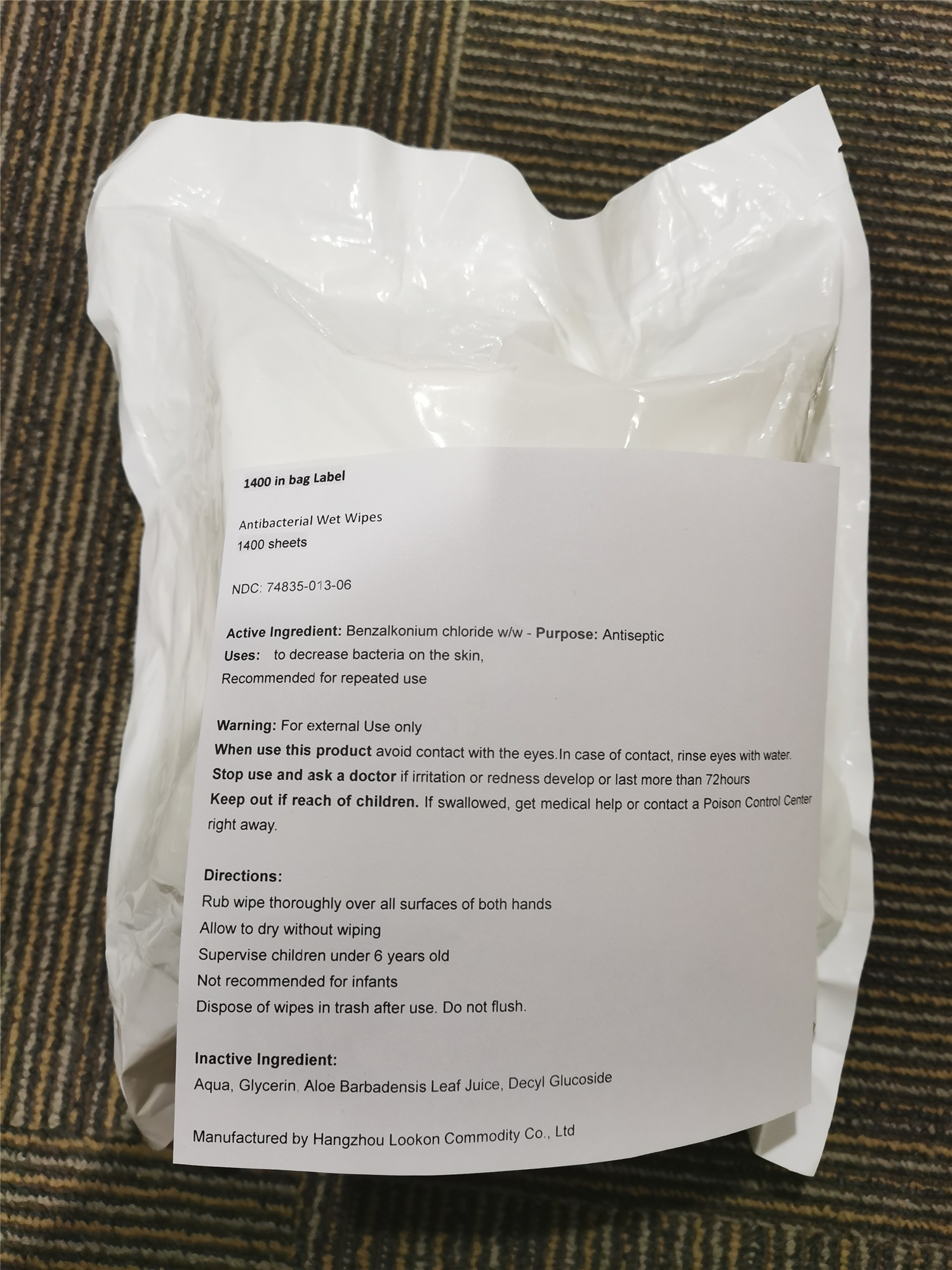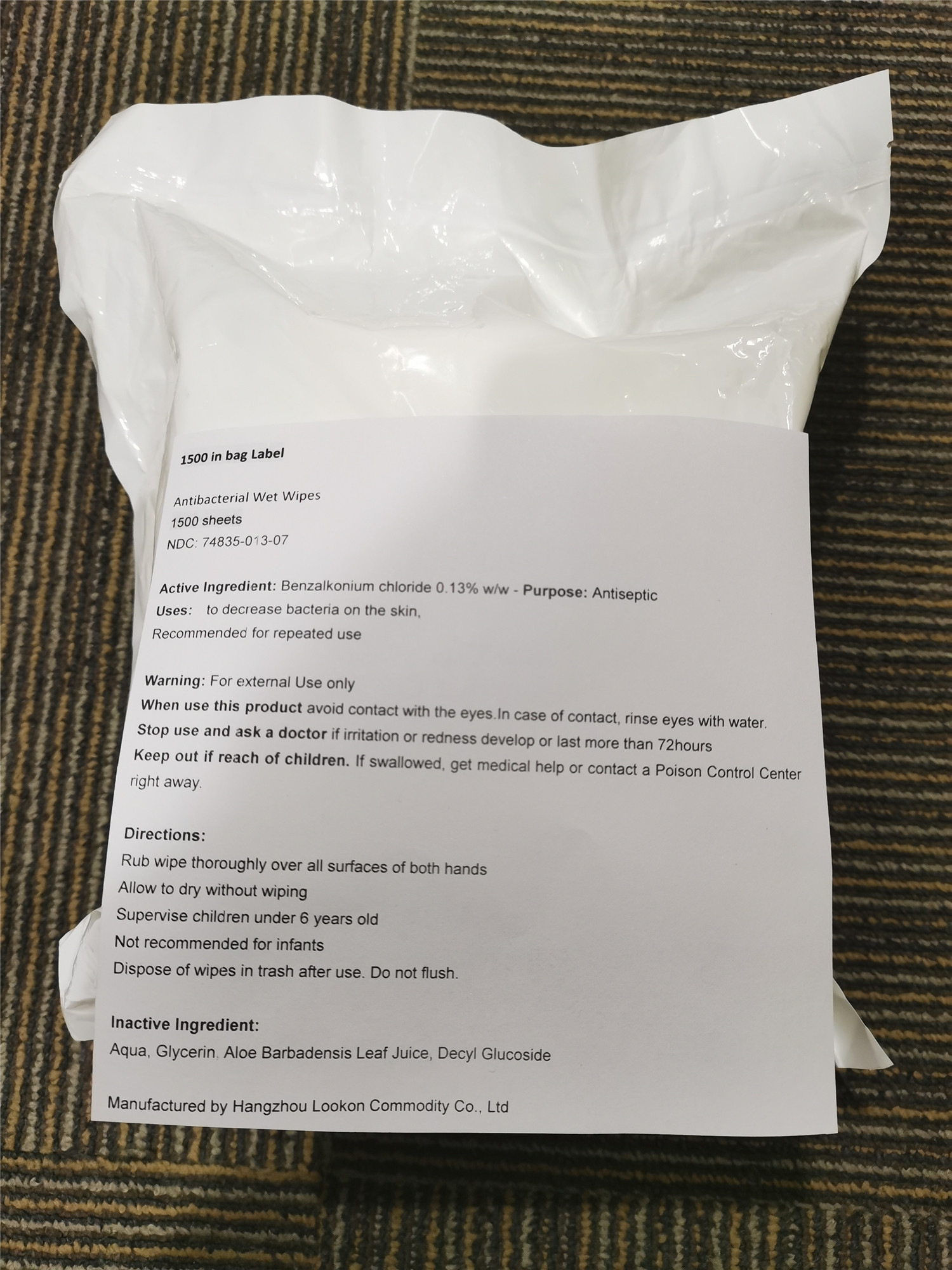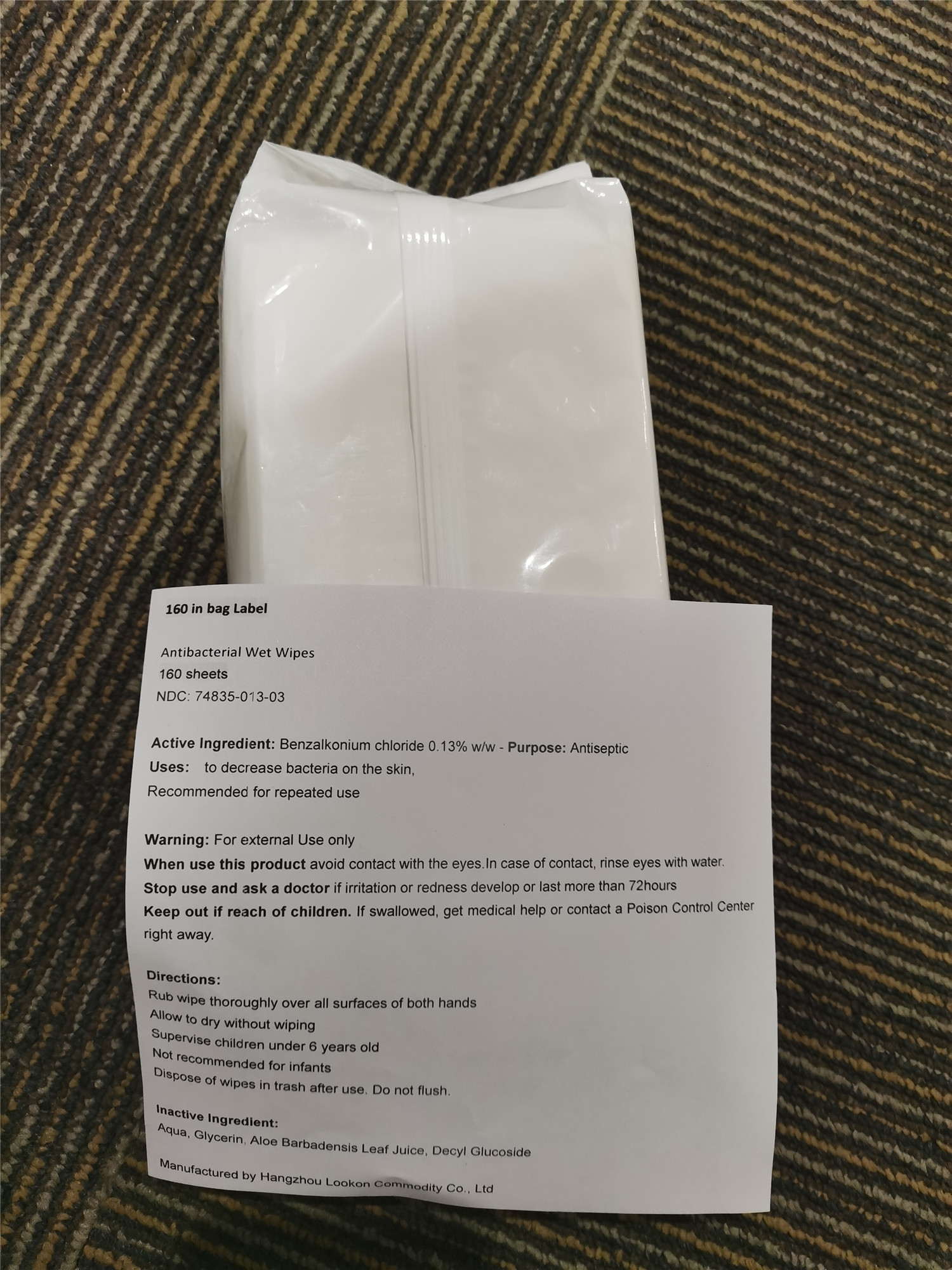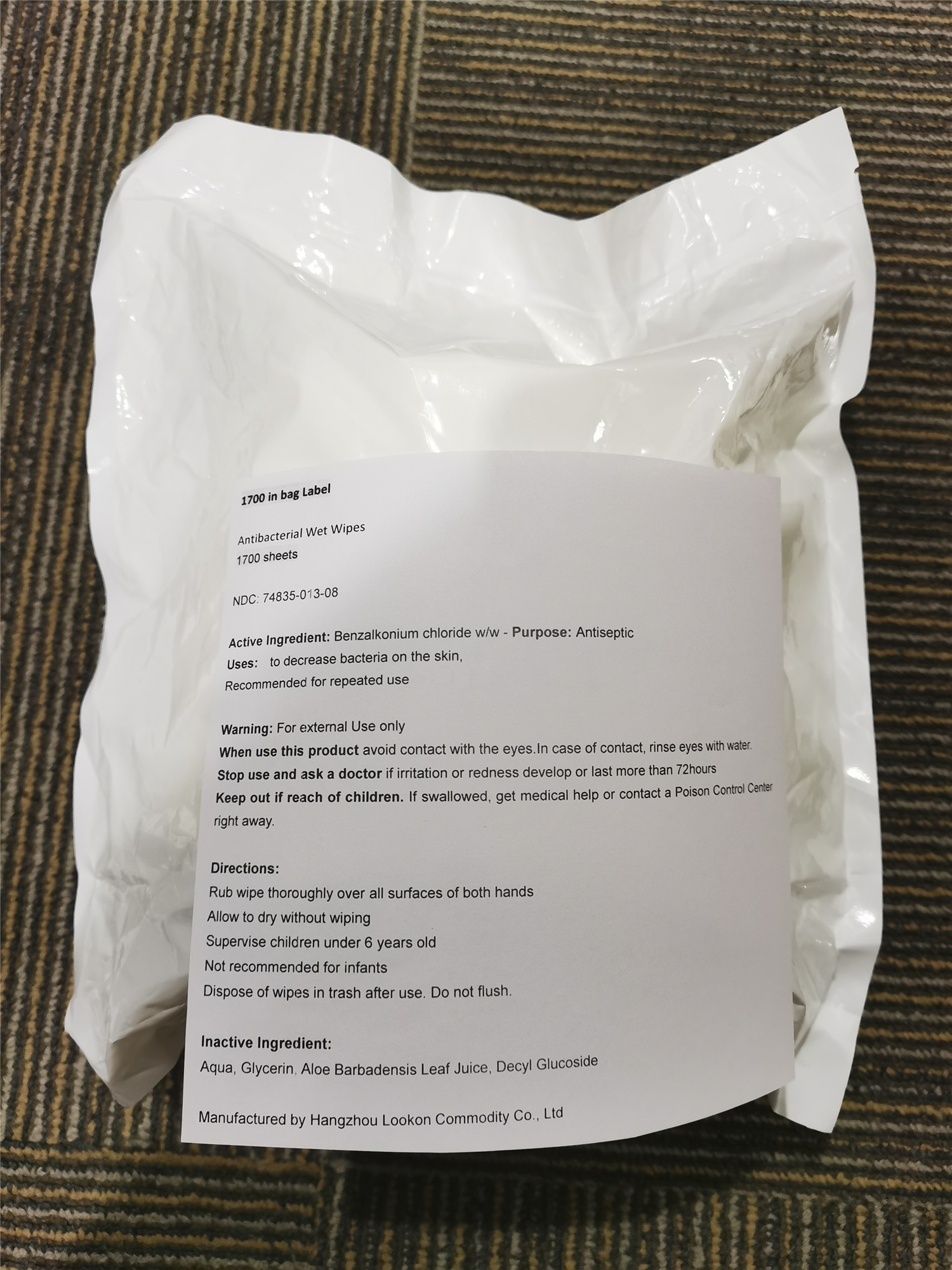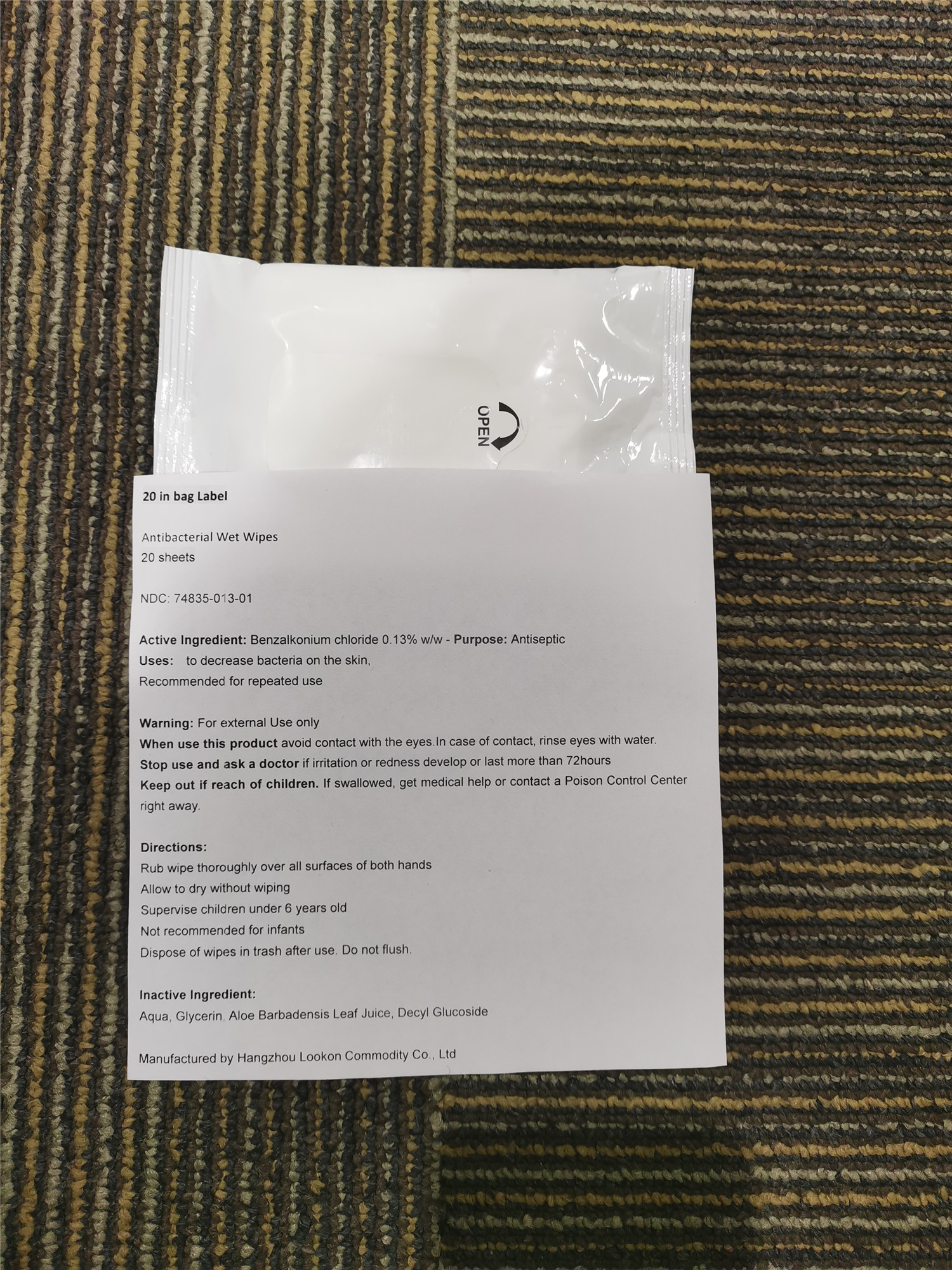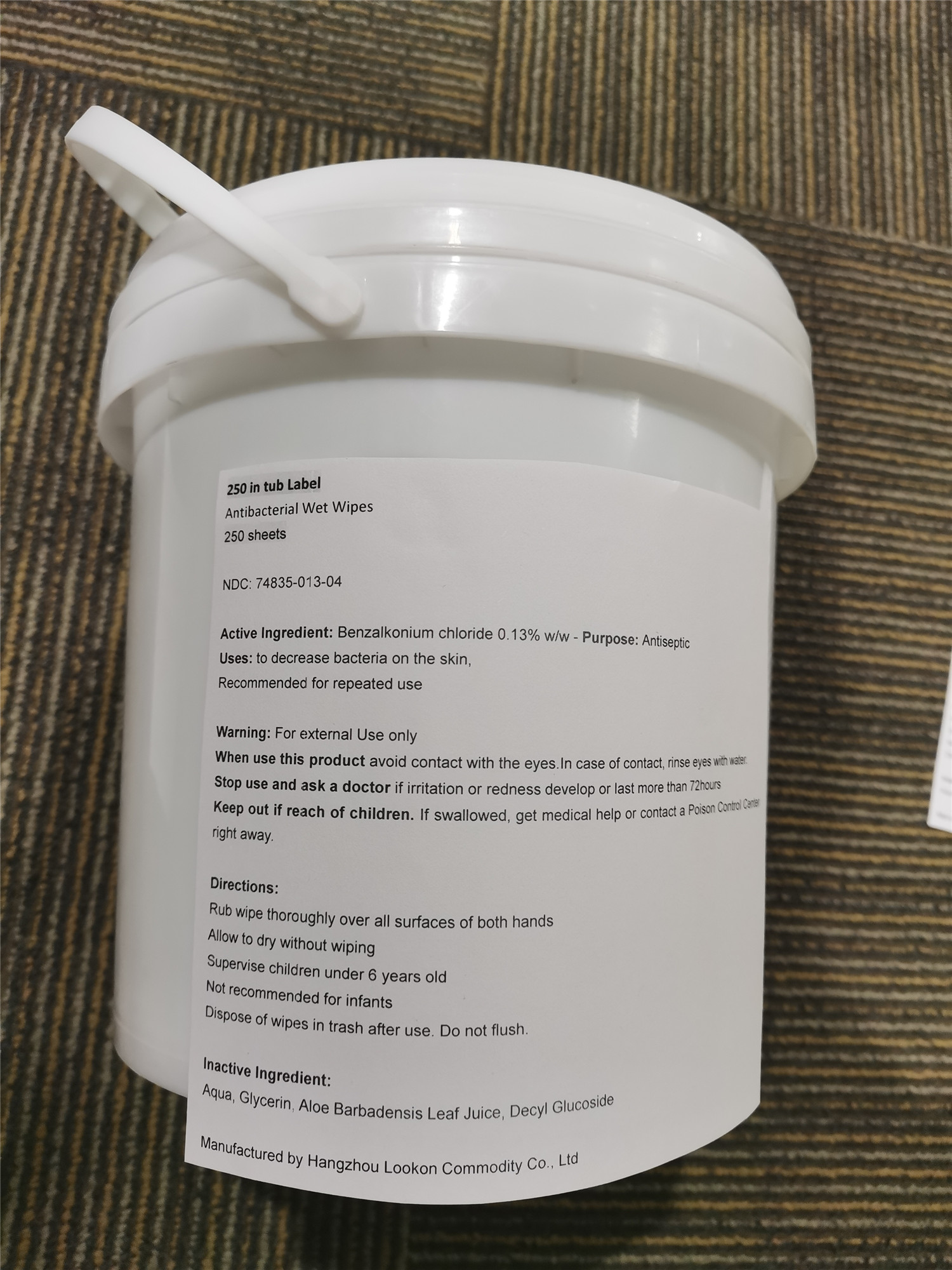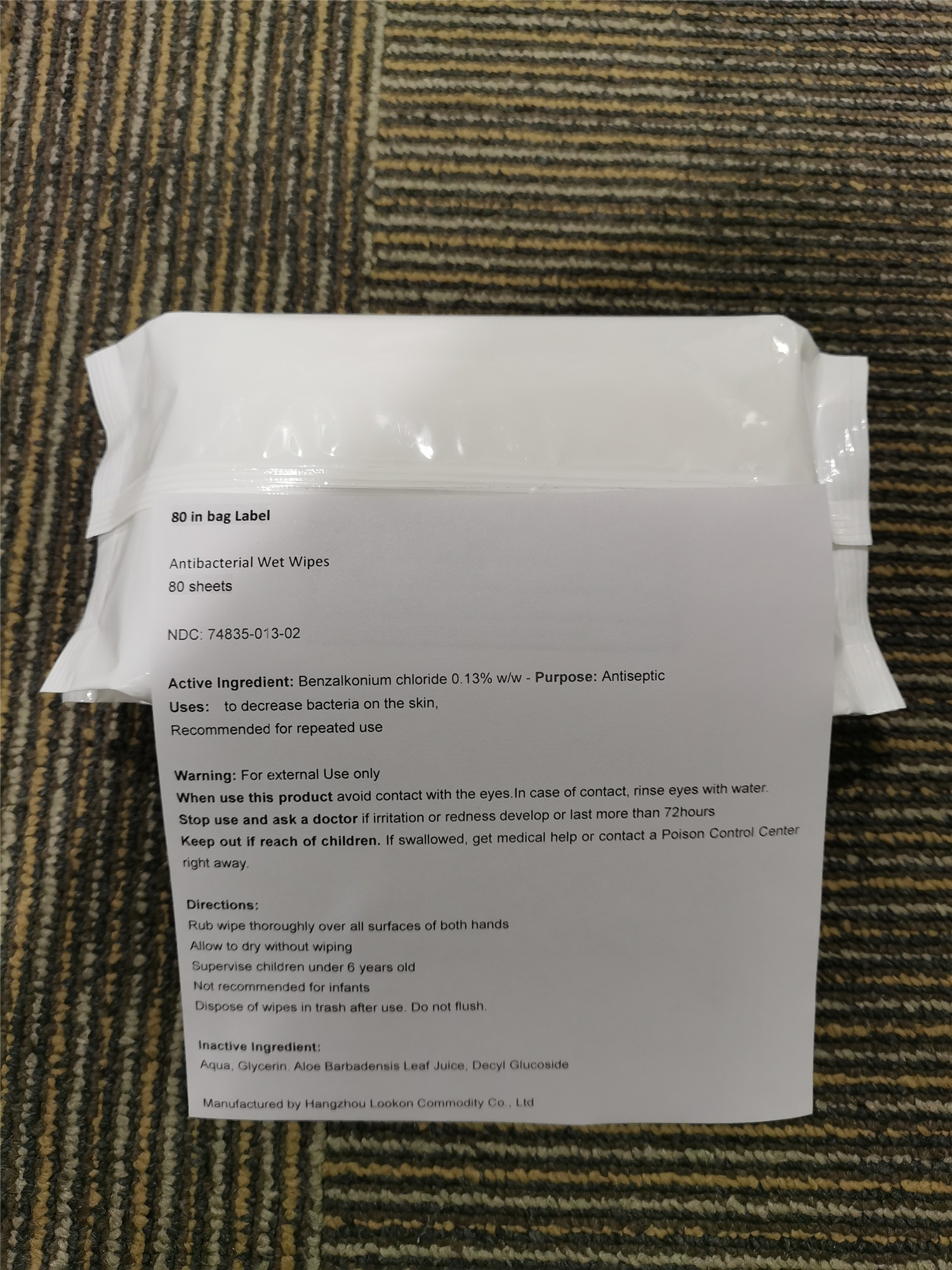 DRUG LABEL: Antibacterial Wet Wipes
NDC: 74835-013 | Form: CLOTH
Manufacturer: Hangzhou Lookon Commodity Co., Ltd.
Category: otc | Type: HUMAN OTC DRUG LABEL
Date: 20221018

ACTIVE INGREDIENTS: BENZALKONIUM CHLORIDE 0.13 g/100 g
INACTIVE INGREDIENTS: ALOE VERA LEAF; WATER; DECYL GLUCOSIDE; GLYCERIN

Antibacterial Wet Wipes

Active Ingredient: Benzalkonium chloride 0.13% w/w

Purpose: Antiseptic

INDICATIONS AND USAGE

Uses: to decrease bacteria on the skin,

Recommended for repeated use

WARNINGS

Warning: For external Use only

When use this product avoid contact with the eyes.In case of contact, rinse eyes with water.

Stop use and ask a doctor if irritation or redness develop or last more than 72hours

Keep out if reach of children. If swallowed, get medical help or contact a Poison Control Center right away.

WHEN USING

When use this product avoid contact with the eyes.In case of contact, rinse eyes with water.

Stop use and ask a doctor if irritation or redness develop or last more than 72hours

KEEP OUT OF REACH OF CHILDREN

Keep out if reach of children. If swallowed, get medical help or contact a Poison Control Center right away.

Directions:

Rub wipe thoroughly over all surfaces of both hands

Allow to dry without wiping

Supervise children under 6 years old

Not recommended for infants

Dispose of wipes in trash after use. Do not flush.

Inactive Ingredient:

Aqua, Glycerin, Aloe Barbadensis Leaf Juice, Decyl Glucoside

PACKAGE LABEL

NDC: 74835-013-01

PACKAGE LABEL

NDC: 74835-013-02

PACKAGE LABEL

NDC: 74835-013-03

PACKAGE LABEL

NDC: 74835-013-04

PACKAGE LABEL

NDC: 74835-013-05

PACKAGE LABEL

NDC: 74835-013-06

PACKAGE LABEL

NDC: 74835-013-07

PACKAGE LABEL

NDC: 74835-013-08